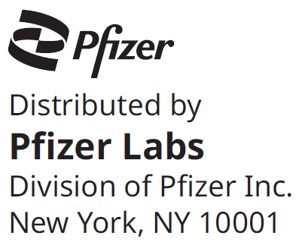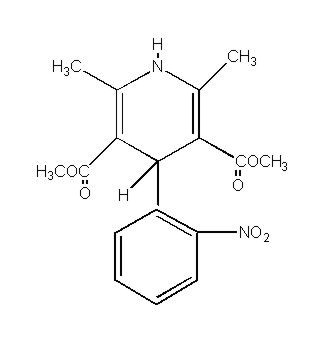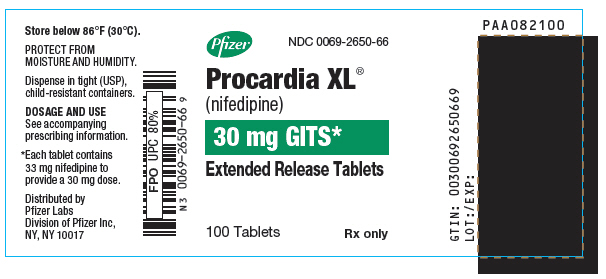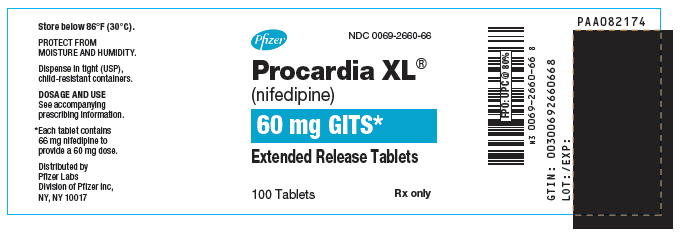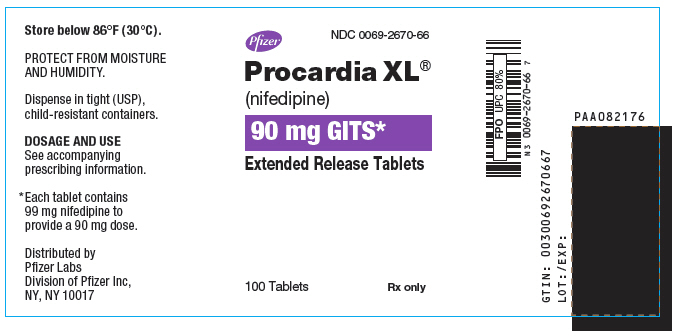 DRUG LABEL: Procardia
NDC: 0069-2650 | Form: TABLET, FILM COATED, EXTENDED RELEASE
Manufacturer: Pfizer Laboratories Div Pfizer Inc
Category: prescription | Type: HUMAN PRESCRIPTION DRUG LABEL
Date: 20251216

ACTIVE INGREDIENTS: NIFEDIPINE 30 mg/1 1
INACTIVE INGREDIENTS: CELLULOSE ACETATE; HYDROXYPROPYL CELLULOSE (1600000 WAMW); HYPROMELLOSE, UNSPECIFIED; MAGNESIUM STEARATE; POLYETHYLENE GLYCOL, UNSPECIFIED; FERRIC OXIDE RED; SODIUM CHLORIDE; TITANIUM DIOXIDE

PROCARDIA XL®
(nifedipine)
Extended Release Tablets
For Oral Use

DESCRIPTION

Nifedipine is a drug belonging to a class of pharmacological agents known as the calcium channel blockers. Nifedipine is 3,5-pyridinedicarboxylic acid, 1,4-dihydro-2,6-dimethyl-4-(2-nitrophenyl)-, dimethyl ester, C17H18N2O6, and has the structural formula:

Nifedipine is a yellow crystalline substance, practically insoluble in water but soluble in ethanol. It has a molecular weight of 346.3. PROCARDIA XL is a registered trademark for Nifedipine GITS. Nifedipine GITS (Gastrointestinal Therapeutic System) Tablet is formulated as a once-a-day controlled-release tablet for oral administration to provide 30, 60, or 90 mg of nifedipine.

Each tablet contains 33 mg nifedipine to provide a 30 mg dose.
Each tablet contains 66 mg nifedipine to provide a 60 mg dose.
Each tablet contains 99 mg nifedipine to provide a 90 mg dose.

Inert ingredients in the formulations are: cellulose acetate; hydroxypropyl cellulose; hypromellose; magnesium stearate; polyethylene glycol; polyethylene oxide; red ferric oxide; sodium chloride; titanium dioxide.

System Components and Performance

PROCARDIA XL® Extended Release Tablet is similar in appearance to a conventional tablet. It consists, however, of a semipermeable membrane surrounding an osmotically active drug core. The core itself is divided into two layers: an "active" layer containing the drug, and a "push" layer containing pharmacologically inert (but osmotically active) components. As water from the gastrointestinal tract enters the tablet, pressure increases in the osmotic layer and "pushes" against the drug layer, releasing drug through the precision laser-drilled tablet orifice in the active layer.

PROCARDIA XL Extended Release Tablet is designed to provide nifedipine at an approximately constant rate over 24 hours. This controlled rate of drug delivery into the gastrointestinal lumen is independent of pH or gastrointestinal motility. PROCARDIA XL depends for its action on the existence of an osmotic gradient between the contents of the bi-layer core and fluid in the gastrointestinal tract. Drug delivery is essentially constant as long as the osmotic gradient remains constant, and then gradually falls to zero. Upon swallowing, the biologically inert components of the tablet remain intact during gastrointestinal transit and are eliminated in the feces as an insoluble shell.

CLINICAL PHARMACOLOGY

Nifedipine is a calcium ion influx inhibitor (slow-channel blocker or calcium ion antagonist) and inhibits the transmembrane influx of calcium ions into cardiac muscle and smooth muscle. The contractile processes of cardiac muscle and vascular smooth muscle are dependent upon the movement of extracellular calcium ions into these cells through specific ion channels. Nifedipine selectively inhibits calcium ion influx across the cell membrane of cardiac muscle and vascular smooth muscle without altering serum calcium concentrations.

Mechanism of Action

A) Angina

The precise mechanisms by which inhibition of calcium influx relieves angina has not been fully determined, but includes at least the following two mechanisms:

1) Relaxation and Prevention of Coronary Artery Spasm

Nifedipine dilates the main coronary arteries and coronary arterioles, both in normal and ischemic regions, and is a potent inhibitor of coronary artery spasm, whether spontaneous or ergonovine-induced. This property increases myocardial oxygen delivery in patients with coronary artery spasm, and is responsible for the effectiveness of nifedipine in vasospastic (Prinzmetal's or variant) angina. Whether this effect plays any role in classical angina is not clear, but studies of exercise tolerance have not shown an increase in the maximum exercise rate-pressure product, a widely accepted measure of oxygen utilization. This suggests that, in general, relief of spasm or dilation of coronary arteries is not an important factor in classical angina.

2) Reduction of Oxygen Utilization

Nifedipine regularly reduces arterial pressure at rest and at a given level of exercise by dilating peripheral arterioles and reducing the total peripheral vascular resistance (afterload) against which the heart works. This unloading of the heart reduces myocardial energy consumption and oxygen requirements, and probably accounts for the effectiveness of nifedipine in chronic stable angina.

B) Hypertension

The mechanism by which nifedipine reduces arterial blood pressure involves peripheral arterial vasodilatation and the resulting reduction in peripheral vascular resistance. The increased peripheral vascular resistance that is an underlying cause of hypertension results from an increase in active tension in the vascular smooth muscle. Studies have demonstrated that the increase in active tension reflects an increase in cytosolic free calcium.

Nifedipine is a peripheral arterial vasodilator which acts directly on vascular smooth muscle. The binding of nifedipine to voltage-dependent and possibly receptor-operated channels in vascular smooth muscle results in an inhibition of calcium influx through these channels. Stores of intracellular calcium in vascular smooth muscle are limited and thus dependent upon the influx of extracellular calcium for contraction to occur. The reduction in calcium influx by nifedipine causes arterial vasodilation and decreased peripheral vascular resistance which results in reduced arterial blood pressure.

Pharmacokinetics and Metabolism

Nifedipine is completely absorbed after oral administration. Plasma drug concentrations rise at a gradual, controlled rate after a PROCARDIA XL Extended Release Tablet dose and reach a plateau at approximately six hours after the first dose. For subsequent doses, relatively constant plasma concentrations at this plateau are maintained with minimal fluctuations over the 24-hour dosing interval. About a four-fold higher fluctuation index (ratio of peak to trough plasma concentration) was observed with the conventional immediate-release PROCARDIA® capsule at t.i.d. dosing than with once daily PROCARDIA XL Extended Release Tablet. At steady-state, the bioavailability of the PROCARDIA XL Extended Release Tablet is 86% relative to PROCARDIA capsules. Administration of the PROCARDIA XL Extended Release Tablet in the presence of food slightly alters the early rate of drug absorption, but does not influence the extent of drug bioavailability. Markedly reduced gastrointestinal retention time over prolonged periods (i.e., short bowel syndrome), however, may influence the pharmacokinetic profile of the drug which could potentially result in lower plasma concentrations. Pharmacokinetics of PROCARDIA XL Extended Release Tablets are linear over the dose range of 30 to 180 mg in that plasma drug concentrations are proportional to dose administered. There was no evidence of dose dumping either in the presence or absence of food for over 150 subjects in pharmacokinetic studies.

Nifedipine is extensively metabolized to highly water-soluble, inactive metabolites, accounting for 60 to 80% of the dose excreted in the urine. The elimination half-life of nifedipine is approximately two hours. Only traces (less than 0.1% of the dose) of unchanged form can be detected in the urine. The remainder is excreted in the feces in metabolized form, most likely as a result of biliary excretion. Thus, the pharmacokinetics of nifedipine are not significantly influenced by the degree of renal impairment. Patients in hemodialysis or chronic ambulatory peritoneal dialysis have not reported significantly altered pharmacokinetics of nifedipine. Since hepatic biotransformation is the predominant route for the disposition of nifedipine, the pharmacokinetics may be altered in patients with chronic liver disease. Patients with hepatic impairment (liver cirrhosis) have a longer disposition half-life and higher bioavailability of nifedipine than healthy volunteers. The degree of serum protein binding of nifedipine is high (92–98%). Protein binding may be greatly reduced in patients with renal or hepatic impairment.

Following intravenous administration, clearance of nifedipine was decreased by 33% in elderly healthy subjects relative to young healthy subjects.

Hemodynamics

Like other slow-channel blockers, nifedipine exerts a negative inotropic effect on isolated myocardial tissue. This is rarely, if ever, seen in intact animals or man, probably because of reflex responses to its vasodilating effects. In man, nifedipine decreases peripheral vascular resistance which leads to a fall in systolic and diastolic pressures, usually minimal in normotensive volunteers (less than 5–10 mm Hg systolic), but sometimes larger. With PROCARDIA XL Extended Release Tablets, these decreases in blood pressure are not accompanied by any significant change in heart rate. Hemodynamic studies in patients with normal ventricular function have generally found a small increase in cardiac index without major effects on ejection fraction, left ventricular end diastolic pressure (LVEDP), or volume (LVEDV). In patients with impaired ventricular function, most acute studies have shown some increase in ejection fraction and reduction in left ventricular filling pressure.

Electrophysiologic Effects

Although, like other members of its class, nifedipine causes a slight depression of sinoatrial node function and atrioventricular conduction in isolated myocardial preparations, such effects have not been seen in studies in intact animals or in man. In formal electrophysiologic studies, predominantly in patients with normal conduction systems, nifedipine has had no tendency to prolong atrioventricular conduction or sinus node recovery time, or to slow sinus rate.

INDICATIONS AND USAGE

I. Vasospastic Angina

PROCARDIA XL is indicated for the management of vasospastic angina confirmed by any of the following criteria: 1) classical pattern of angina at rest accompanied by ST segment elevation, 2) angina or coronary artery spasm provoked by ergonovine, or 3) angiographically demonstrated coronary artery spasm. In those patients who have had angiography, the presence of significant fixed obstructive disease is not incompatible with the diagnosis of vasospastic angina, provided that the above criteria are satisfied. PROCARDIA XL may also be used where the clinical presentation suggests a possible vasospastic component, but where vasospasm has not been confirmed, e.g., where pain has a variable threshold on exertion, or in unstable angina where electrocardiographic findings are compatible with intermittent vasospasm, or when angina is refractory to nitrates and/or adequate doses of beta blockers.

II. Chronic Stable Angina (Classical Effort-Associated Angina)

PROCARDIA XL is indicated for the management of chronic stable angina (effort-associated angina) without evidence of vasospasm in patients who remain symptomatic despite adequate doses of beta blockers and/or organic nitrates or who cannot tolerate those agents.

In chronic stable angina (effort-associated angina), nifedipine has been effective in controlled trials of up to eight weeks duration in reducing angina frequency and increasing exercise tolerance, but confirmation of sustained effectiveness and evaluation of long-term safety in these patients is incomplete.

Controlled studies in small numbers of patients suggest concomitant use of nifedipine and beta-blocking agents may be beneficial in patients with chronic stable angina, but available information is not sufficient to predict with confidence the effects of concurrent treatment, especially in patients with compromised left ventricular function or cardiac conduction abnormalities. When introducing such concomitant therapy, care must be taken to monitor blood pressure closely, since severe hypotension can occur from the combined effects of the drugs (see WARNINGS).

III. Hypertension

PROCARDIA XL is indicated for the treatment of hypertension, to lower blood pressure. Lowering blood pressure reduces the risk of fatal and nonfatal cardiovascular events, primarily strokes and myocardial infarctions. These benefits have been seen in controlled trials of antihypertensive drugs from a wide variety of pharmacologic classes including PROCARDIA XL.

Control of high blood pressure should be part of comprehensive cardiovascular risk management, including, as appropriate, lipid control, diabetes management, antithrombotic therapy, smoking cessation, exercise, and limited sodium intake. Many patients will require more than one drug to achieve blood pressure goals. For specific advice on goals and management, see published guidelines, such as those of the National High Blood Pressure Education Program's Joint National Committee on Prevention, Detection, Evaluation, and Treatment of High Blood Pressure (JNC).

Numerous antihypertensive drugs, from a variety of pharmacologic classes and with different mechanisms of action, have been shown in randomized controlled trials to reduce cardiovascular morbidity and mortality, and it can be concluded that it is blood pressure reduction, and not some other pharmacologic property of the drugs, that is largely responsible for those benefits. The largest and most consistent cardiovascular outcome benefit has been a reduction in the risk of stroke, but reductions in myocardial infarction and cardiovascular mortality also have been seen regularly.

Elevated systolic or diastolic pressure causes increased cardiovascular risk, and the absolute risk increase per mmHg is greater at higher blood pressures, so that even modest reductions of severe hypertension can provide substantial benefit. Relative risk reduction from blood pressure reduction is similar across populations with varying absolute risk, so the absolute benefit is greater in patients who are at higher risk independent of their hypertension (for example, patients with diabetes or hyperlipidemia), and such patients would be expected to benefit from more aggressive treatment to a lower blood pressure goal.

Some antihypertensive drugs have smaller blood pressure effects (as monotherapy) in black patients, and many antihypertensive drugs have additional approved indications and effects (e.g., on angina, heart failure, or diabetic kidney disease). These considerations may guide selection of therapy.

PROCARDIA XL may be used alone or in combination with other antihypertensive agents.

CONTRAINDICATIONS

Known hypersensitivity reaction to nifedipine.

WARNINGS

Excessive Hypotension

Although in most angina patients the hypotensive effect of nifedipine is modest and well tolerated, occasional patients have had excessive and poorly tolerated hypotension. These responses have usually occurred during initial titration or at the time of subsequent upward dosage adjustment, and may be more likely in patients on concomitant beta blockers.

Severe hypotension and/or increased fluid volume requirements have been reported in patients receiving nifedipine together with a beta-blocking agent who underwent coronary artery bypass surgery using high dose fentanyl anesthesia. The interaction with high dose fentanyl appears to be due to the combination of nifedipine and a beta blocker, but the possibility that it may occur with nifedipine alone, with low doses of fentanyl, in other surgical procedures, or with other narcotic analgesics cannot be ruled out. In nifedipine-treated patients where surgery using high dose fentanyl anesthesia is contemplated, the physician should be aware of these potential problems and, if the patient's condition permits, sufficient time (at least 36 hours) should be allowed for nifedipine to be washed out of the body prior to surgery.

The following information should be taken into account in those patients who are being treated for hypertension as well as angina:

Increased Angina and/or Myocardial Infarction

Rarely, patients, particularly those who have severe obstructive coronary artery disease, have developed well documented increased frequency, duration and/or severity of angina or acute myocardial infarction on starting nifedipine or at the time of dosage increase. The mechanism of this effect is not established.

Beta Blocker Withdrawal

It is important to taper beta blockers if possible, rather than stopping them abruptly before beginning nifedipine. Patients recently withdrawn from beta blockers may develop a withdrawal syndrome with increased angina, probably related to increased sensitivity to catecholamines. Initiation of nifedipine treatment will not prevent this occurrence and on occasion has been reported to increase it.

Congestive Heart Failure

Rarely, patients, usually receiving a beta blocker, have developed heart failure after beginning nifedipine. Patients with tight aortic stenosis may be at greater risk for such an event, as the unloading effect of nifedipine would be expected to be of less benefit, owing to the fixed impedance to flow across the aortic valve in these patients.

Gastrointestinal Obstruction Requiring Surgery

There have been rare reports of obstructive symptoms in patients with known strictures in association with the ingestion of PROCARDIA XL. Bezoars can occur in very rare cases and may require surgical intervention.

Cases of serious gastrointestinal obstruction have been identified in patients with no known gastrointestinal disease, including the need for hospitalization and surgical intervention.

Risk factors for a gastrointestinal obstruction identified from post-marketing reports of PROCARDIA XL (GITS tablet formulation) include alteration in gastrointestinal anatomy (e.g., severe gastrointestinal narrowing, colon cancer, small bowel obstruction, bowel resection, gastric bypass, vertical banded gastroplasty, colostomy, diverticulitis, diverticulosis, and inflammatory bowel disease), hypomotility disorders (e.g., constipation, gastroesophageal reflux disease, ileus, obesity, hypothyroidism, and diabetes) and concomitant medications (e.g., H2-histamine blockers, opiates, nonsteroidal anti-inflammatory drugs, laxatives, anticholinergic agents, levothyroxine, and neuromuscular blocking agents).

Gastrointestinal Ulcers

Cases of tablet adherence to the gastrointestinal wall with ulceration have been reported, some requiring hospitalization and intervention.

PRECAUTIONS

General—Hypotension

Because nifedipine decreases peripheral vascular resistance, careful monitoring of blood pressure during the initial administration and titration of nifedipine is suggested. Close observation is especially recommended for patients already taking medications that are known to lower blood pressure (see WARNINGS).

Peripheral Edema

Mild to moderate peripheral edema occurs in a dose dependent manner with an incidence ranging from approximately 10% to about 30% at the highest dose studied (180 mg). It is a localized phenomenon thought to be associated with vasodilation of dependent arterioles and small blood vessels and not due to left ventricular dysfunction or generalized fluid retention. With patients whose angina or hypertension is complicated by congestive heart failure, care should be taken to differentiate this peripheral edema from the effects of increasing left ventricular dysfunction.

Information for Patients

PROCARDIA XL Extended Release Tablets should be swallowed whole. Do not chew, divide or crush tablets. Do not be concerned if you occasionally notice in your stool something that looks like a tablet. In PROCARDIA XL, the medication is contained within a nonabsorbable shell that has been specially designed to slowly release the drug for your body to absorb. When this process is completed, the empty tablet is eliminated from your body.

Laboratory Tests

Rare, usually transient, but occasionally significant elevations of enzymes such as alkaline phosphatase, CPK, LDH, SGOT and SGPT have been noted. The relationship to nifedipine therapy is uncertain in most cases, but probable in some. These laboratory abnormalities have rarely been associated with clinical symptoms; however, cholestasis with or without jaundice has been reported. A small (5.4%) increase in mean alkaline phosphatase was noted in patients treated with PROCARDIA XL. This was an isolated finding not associated with clinical symptoms and it rarely resulted in values which fell outside the normal range. Rare instances of allergic hepatitis have been reported. In controlled studies, PROCARDIA XL did not adversely affect serum uric acid, glucose, or cholesterol. Serum potassium was unchanged in patients receiving PROCARDIA XL in the absence of concomitant diuretic therapy, and slightly decreased in patients receiving concomitant diuretics.

Nifedipine, like other calcium channel blockers, decreases platelet aggregation in vitro. Limited clinical studies have demonstrated a moderate but statistically significant decrease in platelet aggregation and an increase in bleeding time in some nifedipine patients. This is thought to be a function of inhibition of calcium transport across the platelet membrane. No clinical significance for these findings has been demonstrated.

Positive direct Coombs test with/without hemolytic anemia has been reported, but a causal relationship between nifedipine administration and positivity of this laboratory test, including hemolysis, could not be determined.

Although nifedipine has been used safely in patients with renal dysfunction and has been reported to exert a beneficial effect, in certain cases, rare, reversible elevations in BUN and serum creatinine have been reported in patients with preexisting chronic renal insufficiency. The relationship to nifedipine therapy is uncertain in most cases but probable in some.

Drug Interactions

Beta-adrenergic blocking agents

(see INDICATIONS AND USAGE and WARNINGS) Experience in over 1400 patients with PROCARDIA capsules in a noncomparative clinical trial has shown that concomitant administration of nifedipine and beta-blocking agents is usually well tolerated, but there have been occasional literature reports suggesting that the combination may increase the likelihood of congestive heart failure, severe hypotension, or exacerbation of angina.

Long-acting Nitrates

Nifedipine may be safely co-administered with nitrates, but there have been no controlled studies to evaluate the antianginal effectiveness of this combination.

Digitalis

Administration of nifedipine with digoxin increased digoxin levels in nine of twelve normal volunteers. The average increase was 45%. Another investigator found no increase in digoxin levels in thirteen patients with coronary artery disease. In an uncontrolled study of over two hundred patients with congestive heart failure during which digoxin blood levels were not measured, digitalis toxicity was not observed. Since there have been isolated reports of patients with elevated digoxin levels, it is recommended that digoxin levels be monitored when initiating, adjusting, and discontinuing nifedipine to avoid possible over- or under-digitalization.

Coumarin Anticoagulants

There have been rare reports of increased prothrombin time in patients taking coumarin anticoagulants to whom nifedipine was administered. However, the relationship to nifedipine therapy is uncertain.

Cimetidine

A study in six healthy volunteers has shown a significant increase in peak nifedipine plasma levels (80%) and area-under-the-curve (74%), after a one week course of cimetidine at 1000 mg per day and nifedipine at 40 mg per day. Ranitidine produced smaller, non-significant increases. The effect may be mediated by the known inhibition of cimetidine on hepatic cytochrome P-450, the enzyme system probably responsible for the first-pass metabolism of nifedipine. If nifedipine therapy is initiated in a patient currently receiving cimetidine, cautious titration is advised.

Nifedipine is metabolized by CYP3A4. Co-administration of nifedipine with phenytoin, an inducer of CYP3A4, lowers the systemic exposure to nifedipine by approximately 70%. Avoid co-administration of nifedipine with phenytoin or any known CYP3A4 inducer or consider an alternative antihypertensive therapy.

CYP3A inhibitors such as fluconazole, itraconazole, clarithromycin, erythromycin, nefazodone, fluoxetine, saquinavir, indinavir, and nelfinavir may result in increased exposure to nifedipine when co-administered. Careful monitoring and dose adjustment may be necessary; consider initiating nifedipine at the lowest dose available if given concomitantly with these medications.

Other Interactions

Grapefruit Juice

Co-administration of nifedipine with grapefruit juice resulted in approximately a doubling in nifedipine AUC and Cmax with no change in half-life. The increased plasma concentrations most likely result from inhibition of CYP 3A4 related first-pass metabolism. Avoid ingestion of grapefruit and grapefruit juice should be avoided while taking nifedipine.

Carcinogenesis, Mutagenesis, Impairment of Fertility

Nifedipine was administered orally to rats for two years and was not shown to be carcinogenic. When given to rats prior to mating, nifedipine caused reduced fertility at a dose approximately 5 times the maximum recommended human dose. There is a literature report of reversible reduction in the ability of human sperm obtained from a limited number of infertile men taking recommended doses of nifedipine to bind to and fertilize an ovum in vitro. In vivo mutagenicity studies were negative.

Pregnancy

Nifedipine has been shown to produce teratogenic findings in rats and rabbits, including digital anomalies similar to those reported for phenytoin. Digital anomalies have been reported to occur with other members of the dihydropyridine class and are possibly a result of compromised uterine blood flow. Nifedipine administration was associated with a variety of embryotoxic, placentotoxic, and fetotoxic effects, including stunted fetuses (rats, mice, rabbits), rib deformities (mice), cleft palate (mice), small placentas and underdeveloped chorionic villi (monkeys), embryonic and fetal deaths (rats, mice, rabbits), and prolonged pregnancy/decreased neonatal survival (rats; not evaluated in other species). On a mg/kg basis, all of the doses associated with the teratogenic embryotoxic or fetotoxic effects in animals were higher (5 to 50 times) than the maximum recommended human dose of 120 mg/day. On a mg/m^2 basis, some doses were higher and some were lower than the maximum recommended human dose, but all are within an order of magnitude of it. The doses associated with placentotoxic effects in monkeys were equivalent to or lower than the maximum recommended human dose on a mg/m^2 basis.

There are no adequate and well-controlled studies in pregnant women. PROCARDIA XL Extended Release Tablets should be used during pregnancy only if the potential benefit justifies the potential risk.

Lactation

Nifedipine is transferred through breast milk. PROCARDIA XL should be used during breast-feeding only if the potential benefit justifies the potential risk.

Pediatric Use

Safety and effectiveness in pediatric patients have not been established.

Geriatric Use

Age appears to have a significant effect on the pharmacokinetics of nifedipine. The clearance is decreased resulting in a higher AUC in the elderly. These changes are not due to changes in renal function (see CLINICAL PHARMACOLOGY, Pharmacokinetics).

ADVERSE EXPERIENCES

Over 1000 patients from both controlled and open trials with PROCARDIA XL Extended Release Tablets in hypertension and angina were included in the evaluation of adverse experiences. All side effects reported during PROCARDIA XL Extended Release Tablet therapy were tabulated independent of their causal relation to medication. The most common side effect reported with PROCARDIA XL was edema which was dose related and ranged in frequency from approximately 10% to about 30% at the highest dose studied (180 mg). Other common adverse experiences reported in placebo-controlled trials include:

Adverse Effect | PROCARDIA XL (%) (N=707) | Placebo (%) (N=266)
Headache | 15.8 | 9.8
Fatigue | 5.9 | 4.1
Dizziness | 4.1 | 4.5
Constipation | 3.3 | 2.3
Nausea | 3.3 | 1.9

Of these, only edema and headache were more common in PROCARDIA XL patients than placebo patients.

The following adverse reactions occurred with an incidence of less than 3.0%. With the exception of leg cramps, the incidence of these side effects was similar to that of placebo alone.

Body as a Whole/Systemic: asthenia, flushing, pain
Cardiovascular: palpitations
Central Nervous System: insomnia, nervousness, paresthesia, somnolence
Dermatologic: pruritus, rash
Gastrointestinal: abdominal pain, diarrhea, dry mouth, dyspepsia, flatulence
Musculoskeletal: arthralgia, leg cramps
Respiratory: chest pain (nonspecific), dyspnea
Urogenital: impotence, polyuria

Other adverse reactions were reported sporadically with an incidence of 1.0% or less. These include:

Body as a Whole/Systemic: face edema, fever, hot flashes, malaise, periorbital edema, rigors
Cardiovascular: arrhythmia, hypotension, increased angina, tachycardia, syncope
Central Nervous System: anxiety, ataxia, decreased libido, depression, hypertonia, hypoesthesia, migraine, paroniria, tremor, vertigo
Dermatologic: alopecia, increased sweating, urticaria, purpura
Gastrointestinal: eructation, gastroesophageal reflux, gum hyperplasia, melena, vomiting, weight increase
Musculoskeletal: back pain, gout, myalgias
Respiratory: coughing, epistaxis, upper respiratory tract infection, respiratory disorder, sinusitis
Special Senses: abnormal lacrimation, abnormal vision, taste perversion, tinnitus
Urogenital/Reproductive: breast pain, dysuria, hematuria, nocturia

Adverse experiences which occurred in less than 1 in 1000 patients cannot be distinguished from concurrent disease states or medications.

The following adverse experiences, reported in less than 1% of patients, occurred under conditions (e.g., open trials, marketing experience) where a causal relationship is uncertain: gastrointestinal irritation, gastrointestinal bleeding, gynecomastia.

Gastrointestinal obstruction resulting in hospitalization and surgery, including the need for bezoar removal, has occurred in association with PROCARDIA XL, even in patients with no prior history of gastrointestinal disease (see WARNINGS).

Cases of tablet adherence to the gastrointestinal wall with ulceration have been reported, some requiring hospitalization and intervention.

In multiple-dose U.S. and foreign controlled studies with nifedipine capsules in which adverse reactions were reported spontaneously, adverse effects were frequent but generally not serious and rarely required discontinuation of therapy or dosage adjustment. Most were expected consequences of the vasodilator effects of nifedipine.

Adverse Effect | PROCARDIA CAPSULES (%) (N=226) | Placebo (%) (N=235)
Dizziness, lightheadedness, giddiness | 27 | 15
Flushing, heat sensation | 25 | 8
Headache | 23 | 20
Weakness | 12 | 10
Nausea, heartburn | 11 | 8
Muscle cramps, tremor | 8 | 3
Peripheral edema | 7 | 1
Nervousness, mood changes | 7 | 4
Palpitations | 7 | 5
Dyspnea, cough, wheezing | 6 | 3
Nasal congestion, sore throat | 6 | 8

There is also a large uncontrolled experience in over 2100 patients in the United States. Most of the patients had vasospastic or resistant angina pectoris, and about half had concomitant treatment with beta-adrenergic blocking agents. The relatively common adverse events were similar in nature to those seen with PROCARDIA XL.

In addition, more serious adverse events were observed, not readily distinguishable from the natural history of the disease in these patients. It remains possible, however, that some or many of these events were drug related. Myocardial infarction occurred in about 4% of patients and congestive heart failure or pulmonary edema in about 2%. Ventricular arrhythmias or conduction disturbances each occurred in fewer than 0.5% of patients.

In a subgroup of over 1000 patients receiving PROCARDIA with concomitant beta blocker therapy, the pattern and incidence of adverse experiences was not different from that of the entire group of PROCARDIA-treated patients (see PRECAUTIONS).

In a subgroup of approximately 250 patients with a diagnosis of congestive heart failure as well as angina, dizziness or lightheadedness, peripheral edema, headache, or flushing each occurred in one in eight patients. Hypotension occurred in about one in 20 patients. Syncope occurred in approximately one patient in 250. Myocardial infarction or symptoms of congestive heart failure each occurred in about one patient in 15. Atrial or ventricular dysrhythmias each occurred in about one patient in 150.

In post-marketing experience, there have been rare reports of exfoliative dermatitis caused by nifedipine. There have been rare reports of exfoliative or bullous skin adverse events (such as erythema multiforme, Stevens-Johnson Syndrome, and toxic epidermal necrolysis) and photosensitivity reactions. Acute generalized exanthematous pustulosis also has been reported.

OVERDOSAGE

Experience with nifedipine overdosage is limited. Generally, overdosage with nifedipine leading to pronounced hypotension calls for active cardiovascular support, including monitoring of cardiovascular and respiratory function, elevation of extremities, judicious use of calcium infusion, pressor agents, and fluids. Clearance of nifedipine would be expected to be prolonged in patients with impaired liver function. Since nifedipine is highly protein-bound, dialysis is not likely to be of any benefit.

There has been one reported case of massive overdosage with PROCARDIA XL Extended Release Tablets. The main effects of ingestion of approximately 4800 mg of PROCARDIA XL in a young man attempting suicide as a result of cocaine-induced depression was initial dizziness, palpitations, flushing, and nervousness. Within several hours of ingestion, nausea, vomiting, and generalized edema developed. No significant hypotension was apparent at presentation, 18 hours post-ingestion. Electrolyte abnormalities consisted of a mild, transient elevation of serum creatinine, and modest elevations of LDH and CPK, but normal SGOT. Vital signs remained stable, no electrocardiographic abnormalities were noted, and renal function returned to normal within 24 to 48 hours with routine supportive measures alone. No prolonged sequelae were observed.

The effect of a single 900 mg ingestion of PROCARDIA capsules in a depressed anginal patient also on tricyclic antidepressants was loss of consciousness within 30 minutes of ingestion, and profound hypotension, which responded to calcium infusion, pressor agents, and fluid replacement. A variety of ECG abnormalities were seen in this patient with a history of bundle branch block, including sinus bradycardia and varying degrees of AV block. These dictated the prophylactic placement of a temporary ventricular pacemaker, but otherwise resolved spontaneously. Significant hyperglycemia was seen initially in this patient, but plasma glucose levels rapidly normalized without further treatment.

A young hypertensive patient with advanced renal failure ingested 280 mg of PROCARDIA capsules at one time, with resulting marked hypotension responding to calcium infusion and fluids. No AV conduction abnormalities, arrhythmias, or pronounced changes in heart rate were noted, nor was there any further deterioration in renal function.

DOSAGE AND ADMINISTRATION

Dosage must be adjusted according to each patient's needs. Therapy for either hypertension or angina should be initiated with 30 or 60 mg once daily. PROCARDIA XL Extended Release Tablets should be swallowed whole and should not be bitten or divided. In general, titration should proceed over a 7–14 day period so that the physician can fully assess the response to each dose level and monitor blood pressure before proceeding to higher doses. Since steady-state plasma levels are achieved on the second day of dosing, titration may proceed more rapidly, if symptoms so warrant, provided the patient is assessed frequently. Titration to doses above 120 mg are not recommended.

Angina patients controlled on PROCARDIA capsules alone or in combination with other antianginal medications may be safely switched to PROCARDIA XL Extended Release Tablets at the nearest equivalent total daily dose (e.g., 30 mg t.i.d. of PROCARDIA capsules may be changed to 90 mg once daily of PROCARDIA XL Extended Release Tablets). Subsequent titration to higher or lower doses may be necessary and should be initiated as clinically warranted. Experience with doses greater than 90 mg in patients with angina is limited. Therefore, doses greater than 90 mg should be used with caution and only when clinically warranted.

Avoid co-administration of nifedipine with grapefruit juice (see CLINICAL PHARMACOLOGY and PRECAUTIONS: Other Interactions).

No "rebound effect" has been observed upon discontinuation of PROCARDIA XL Extended Release Tablets. However, if discontinuation of nifedipine is necessary, sound clinical practice suggests that the dosage should be decreased gradually with close physician supervision.

Care should be taken when dispensing PROCARDIA XL to assure that the extended release dosage form has been prescribed.

Co-Administration with Other Antianginal Drugs

Sublingual nitroglycerin may be taken as required for the control of acute manifestations of angina, particularly during nifedipine titration. See PRECAUTIONS, Drug Interactions, for information on co-administration of nifedipine with beta blockers or long-acting nitrates.

HOW SUPPLIED

PROCARDIA XL Extended Release Tablets are supplied to provide 30 mg, 60 mg and 90 mg round, biconvex, rose-pink, film-coated tablets in:

Bottles of 100: | 30 mg | (NDC 0069-2650-66)
 | 60 mg | (NDC 0069-2660-66)
 | 90 mg | (NDC 0069-2670-66)
Bottles of 300: | 30 mg | (NDC 0069-2650-72)
 | 60 mg | (NDC 0069-2660-72)

STORAGE AND HANDLING

Store below 86°F (30°C).

Protect from moisture and humidity.

LAB-0176-13.0
Revised November 2023

PRINCIPAL DISPLAY PANEL - 30 mg Tablet Bottle Label

Pfizer
NDC 0069-2650-66

Procardia XL®
(nifedipine)

30 mg GITS*

Extended Release Tablets

100 Tablets
Rx only

PRINCIPAL DISPLAY PANEL - 60 mg Tablet Bottle Label

Pfizer
NDC 0069-2660-66

Procardia XL®
(nifedipine)

60 mg GITS*

Extended Release Tablets

100 Tablets
Rx only

PRINCIPAL DISPLAY PANEL - 90 mg Tablet Bottle Label

Pfizer
NDC 0069-2670-66

Procardia XL®
(nifedipine)

90 mg GITS*

Extended Release Tablets

100 Tablets
Rx only